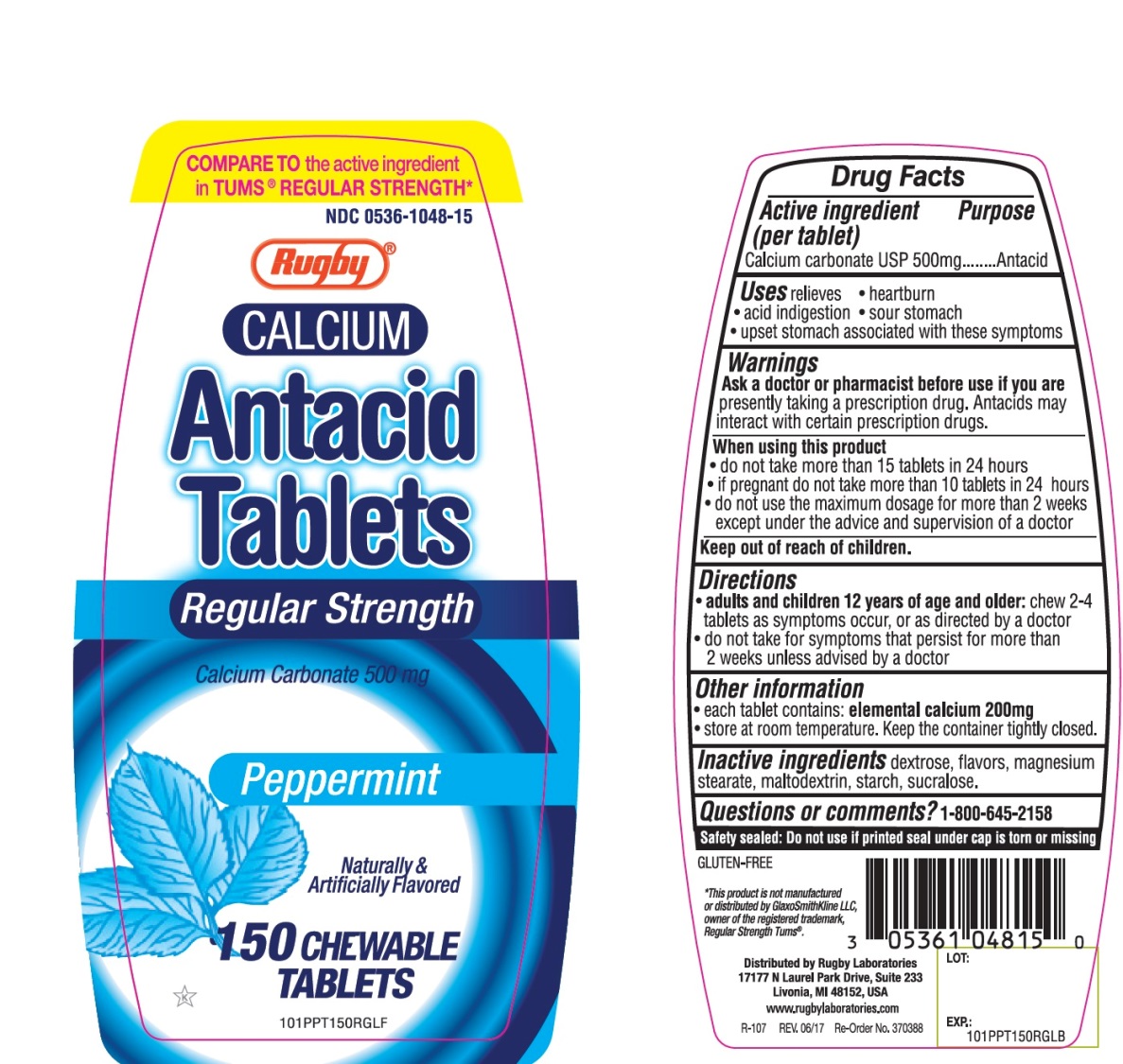 DRUG LABEL: Rugby
NDC: 0536-1048 | Form: TABLET, CHEWABLE
Manufacturer: Rugby Laboratories
Category: otc | Type: HUMAN OTC DRUG LABEL
Date: 20251025

ACTIVE INGREDIENTS: CALCIUM CARBONATE 500 mg/1 1
INACTIVE INGREDIENTS: DEXTROSE, UNSPECIFIED FORM; MAGNESIUM STEARATE; MALTODEXTRIN; STARCH, CORN; SUCRALOSE

Rugby Antacid Regular Strength 150 Chewable Tablets

Active ingredient (Per tablet)

Calcium Carbonate USP 500mg

Purpose

Antacid

Uses

relieves:

- heartburn
- acid indigestion
- sour stomach
- upset stomach associated with these symptoms

Warnings

Ask a doctor or pharmacist before use if you arepresently taking a prescription drug. Antacids may interact with certain prescription drugs.

When using this product

- do not take more than 15 tablets in 24 hours
- if pregnant do not take more than 10 tablets in 24 hours
- do not use the maximum dosage for more than 2 weeks except under the advice and supervision of a doctor

Directions

- adults and children 12 years of age and over:Chew 2-4 tablets as symptoms occur, or as directed by a doctor.
- do not take for symptoms that persist for more than 2 weeks unless advised by a doctor

Other Information

- each tablet contains : elemental calcium 200mg
- Store at room temperature. Keep the container tightly closed.

Inactive ingredients

dextrose, flavors, magnesium stearate, maltodextrin, starch , sucralose

Question or comments?

1-800-645-2158

Safety sealed: Do not use if printed seal under cap is torn or missing

Package/Label Principal Display Panel

COMPARE To the active ingredient in TUMS® REGULAR STRENGTH*

NDC 0536-1048-15

Rugby

CALCIUM

Antacid Tablets

Regular Strength

Calcium Carbonate 500 mg

Peppermint

Naturally & Artificially Flavored

150 Chewable Tablets

GLUTEN-FREE

*This product is not manufactured

or distributed by GlaxoSmithKline LLC,

owner of the registered trademark, Regular Strength Tums©

Distributed by Rugby Laboratories

17177 N Laurel Park Drive, Suite 233

Livonia, MI 48150, USA

www.rugbylaboratories.com